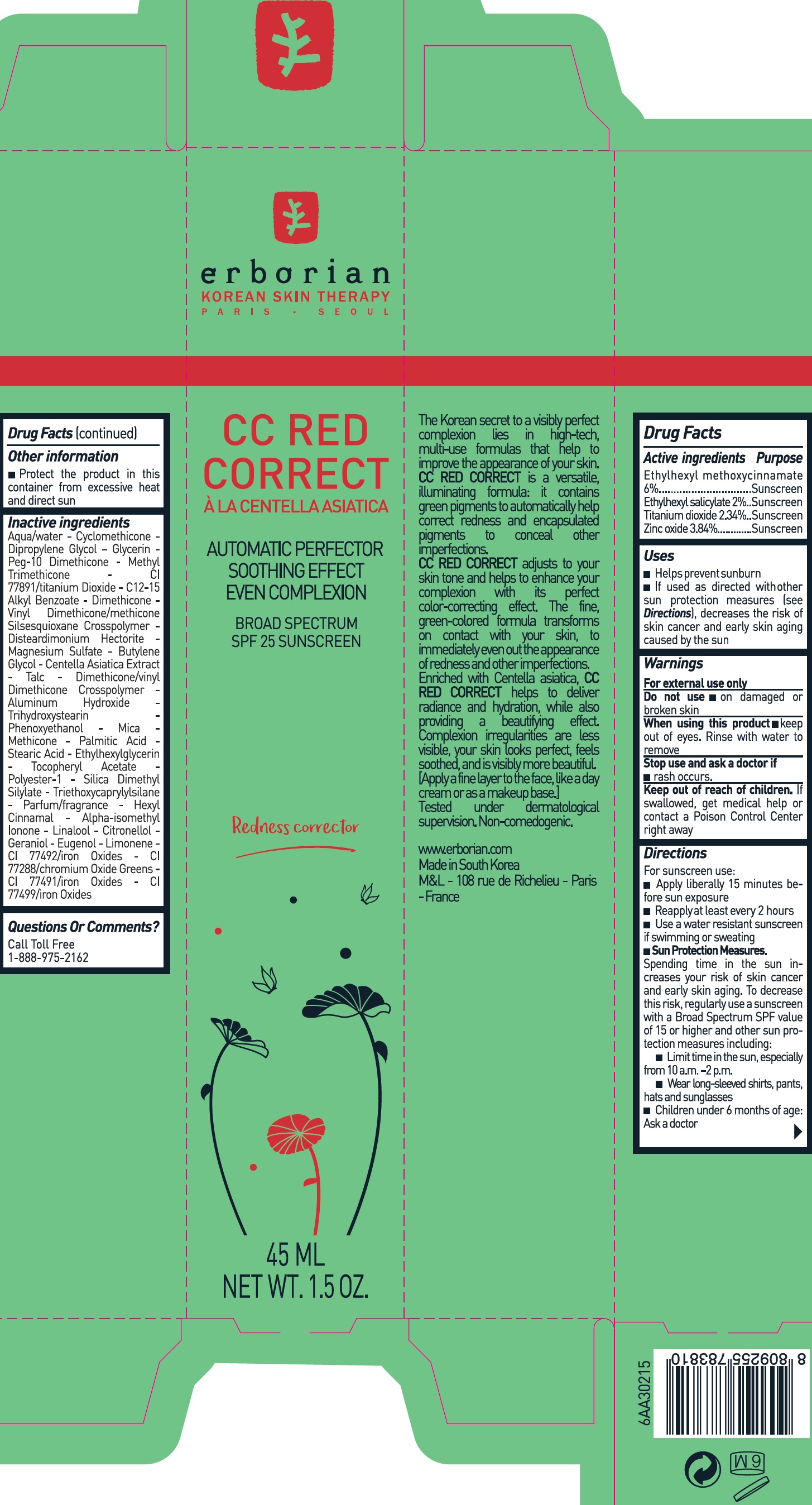 DRUG LABEL: ERBORIAN CC RED CORRECT
NDC: 83573-100 | Form: CREAM
Manufacturer: Kolmask Co., Ld.
Category: otc | Type: HUMAN OTC DRUG LABEL
Date: 20250918

ACTIVE INGREDIENTS: OCTINOXATE 60 mg/1 mL; TITANIUM DIOXIDE 23.4 mg/1 mL; ZINC OXIDE 38.4 mg/1 mL; OCTISALATE 20 mg/1 mL
INACTIVE INGREDIENTS: STEARIC ACID; FERRIC OXIDE RED; PEG-10 DIMETHICONE (600 CST); ALKYL (C12-15) BENZOATE; DIMETHICONE; VINYL DIMETHICONE/METHICONE SILSESQUIOXANE CROSSPOLYMER; DISTEARDIMONIUM HECTORITE; MAGNESIUM SULFATE, UNSPECIFIED FORM; ALUMINUM HYDROXIDE; DIPROPYLENE GLYCOL; PALMITIC ACID; POLYESTER-10; TRIETHOXYCAPRYLYLSILANE; .BETA.-CITRONELLOL, (R)-; .ALPHA.-HEXYLCINNAMALDEHYDE; EUGENOL; PHENOXYETHANOL; CHROMIC OXIDE; CENTELLA ASIATICA; TRIHYDROXYSTEARIN; GLYCERIN; MICA; ETHYLHEXYLGLYCERIN; GERANIOL; LIMONENE, (+)-; FERRIC OXIDE YELLOW; FERROSOFERRIC OXIDE; WATER; CYCLOMETHICONE; SILICA DIMETHYL SILYLATE; ISOMETHYL-.ALPHA.-IONONE; METHYL TRIMETHICONE; BUTYLENE GLYCOL; TALC; METHICONE (20 CST); LINALOOL, (+/-)-

ERBORIAN - CC RED CORRECT SPF25

Drug Facts

Active ingredients

Ethylhexyl methoxycinnamate 6%

Ethylhexyl salicylate 2%

Titanium Dioxide 2.34%

Zinc oxide 3.84%

PURPOSE

Sunscreen

DOSAGE AND ADMINISTRATION

For sunscreen use:

Apply liberally 15 minutes before sun exposure.

Reapply at least every 2 hours

Use a water resistant sunscreen if swimming or sweating

Sun Protection Meausres. Spending time in the sun incerases your risk of skin cancer and early skin aging. To decrease this risk, regularly use a sunscreen with a Broad Spectrum SPF value of 15 or higher and other sun protection measures including:

Limit time in the sun, especially from 10 a.m. - 2 p.m.

Wear long-sleeved shirts, pants, hats and sunglasses

Children under 6 months of age: Ask a doctor.

DO NOT USE

on damaged or broken skin

When using this product

keep out of eyes. Rinse with water to remove

Stop use and ask a doctor if

rash occurs

KEEP OUT OF REACH OF CHILDREN

If swallowed, get medical help or contact a Poison Control Center right away.

Directions

For sunscreen use:
Apply liberally 15 minutes before sun exposure.
Reapply at least every 2 hours
Use a water resistant sunscreen if swimming or sweating
Sun Protection Meausres. Spending time in the sun incerases your risk of skin cancer and early skin aging. To decrease this risk, regularly use a sunscreen with a Broad Spectrum SPF value of 15 or higher and other sun protection measures including:
Limit time in the sun, especially from 10 a.m. - 2 p.m.
Wear long-sleeved shirts, pants, hats and sunglasses
Children under 6 months of age: Ask a doctor.

INACTIVE INGREDIENT

Aqua/water - Cyclomethicone - Dipropylene Glycol - Glycerin - Peg-10 Dimethicone - Methyl Trimethicone - CI 77891/titanium Dioxide - C12-15 Alkyl Benzoate - Dimethicone - Vinyl Dimethicone/methicone Silsesquioxane Crosspolymer - Disteardimonium Hectorite - Magnesium Sulfate - Butylene Glycol - Centella Asiatica Extract - Talc - Dimethicone/Vinyl Dimethicone Crosspolymer - Aluminum Hydroxide - Trihydroxystearn - Phenoxyethanol - Mica - Methicone - Palmitic Acid - Stearic acid - Ethylhexylglycerin - Tocopheryl Acetate - Polyester-1 - Silica Dimethyl Silylate - Triethoxycaprylylsilane - Parfum/Fragrance - Hexyl Cinnamal - Alpha-Isomethyl Ionone - Linalool - Citronellol - Geraniol - Eugenol - Limonene - CI 77492/Iron Oxides - CI 77288/chormium Oxide Greens - CI 77491/Iron Oxides - CI77499/Iron Oxides

QUESTIONS

Call toll free 1-888-975-2162

INDICATIONS AND USAGE

Sun Protection Meausres. Spending time in the sun incerases your risk of skin cancer and early skin aging. To decrease this risk, regularly use a sunscreen with a Broad Spectrum SPF value of 15 or higher and other sun protection measures including:

Limit time in the sun, especially from 10 a.m. - 2 p.m.

Wear long-sleeved shirts, pants, hats and sunglasses

Children under 6 months of age: Ask a doctor.